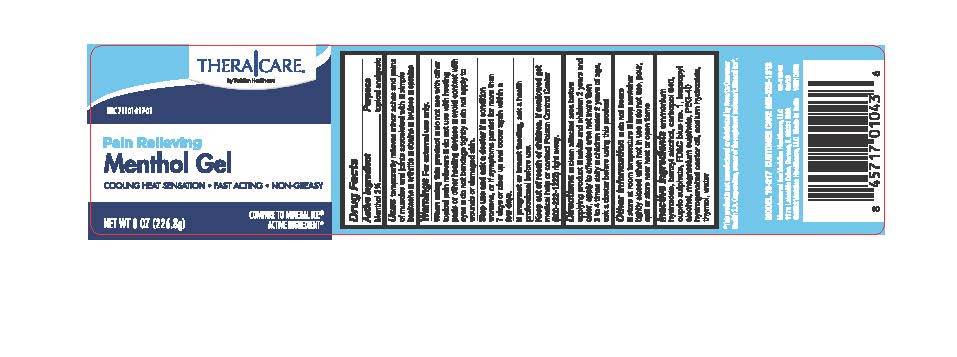 DRUG LABEL: Theracare Ice Blue Gel
NDC: 71101-217 | Form: GEL
Manufacturer: Veridian Healthcare
Category: otc | Type: HUMAN OTC DRUG LABEL
Date: 20241218

ACTIVE INGREDIENTS: MENTHOL 20 mg/1 g
INACTIVE INGREDIENTS: POLYOXYL 40 HYDROGENATED CASTOR OIL; BENZYL ALCOHOL; FD&C BLUE NO. 1; AMMONIA; CARBOMER 940; CUPRIC SULFATE; ISOPROPYL ALCOHOL; MAGNESIUM SULFATE, UNSPECIFIED FORM; SODIUM HYDROXIDE; THYMOL; WATER

Theracare Ice Blue Gel

Active ingredient

Menthol 2%

Purpose

Topical analgesic

Uses

● temporarily relieves minor aches and pains of muscles and joints associated with:

● simple backache

● arthritis

● strains

● bruises

● sprains

Warnings

For external use only

When Using this product

- with other topical pain relievers
- with heating pads or heating devices
- avoid contact with eyes
- do not bandage tightly
- do not apply to wounds or damage skin

Stop use and ask a doctor if

- condition worsens or symptoms persist for more than 7 days or clear up and occur again within a few days

If pregnant or breast-feeding

ask a health professional before use

Keep Out of Reach of Children

If swallowed, get medical help or contact a Poison Control Center (800-222-1222) right away.

Directions

- clean affected area before applying product
- adults and children 2 years of age and older: apply to affected area not more than 3 to 4 times daily
- children under 2 years of age: ask a doctor before using this product

Other information

- do not freeze
- store at room temperature
- keep container tightly closed when not in use
- do not use, pour, spill, or store near heat or open flame

Inactive ingredients

ammonium hydroxide, benzyl alcohol, carbopor 940, cupric sulfate, FD&C blue no. 1, isopropyl alcohol, magnesium sulfate, PEG-40 hydrogenated castor oil, sodium hydroxide, thymol, water

Questions or comments?

Customer care 866-326-1313